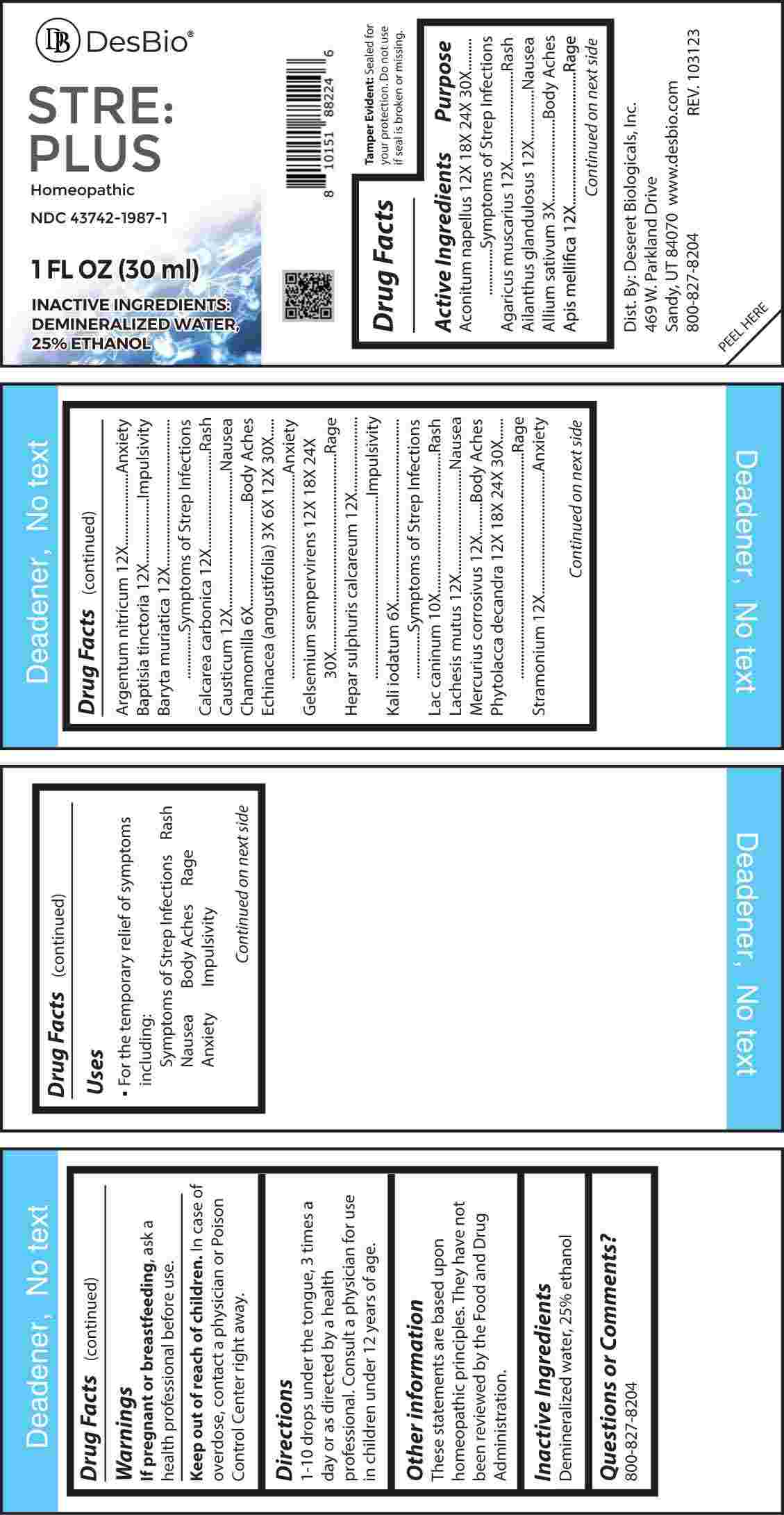 DRUG LABEL: STRE PLUS
NDC: 43742-1987 | Form: LIQUID
Manufacturer: Deseret Biologicals, Inc.
Category: homeopathic | Type: HUMAN OTC DRUG LABEL
Date: 20240222

ACTIVE INGREDIENTS: GARLIC 3 [hp_X]/1 mL; ECHINACEA ANGUSTIFOLIA WHOLE 3 [hp_X]/1 mL; MATRICARIA CHAMOMILLA WHOLE 6 [hp_X]/1 mL; POTASSIUM IODIDE 6 [hp_X]/1 mL; CANIS LUPUS FAMILIARIS MILK 10 [hp_X]/1 mL; AMANITA MUSCARIA FRUITING BODY 12 [hp_X]/1 mL; AILANTHUS ALTISSIMA FLOWERING TWIG 12 [hp_X]/1 mL; APIS MELLIFERA 12 [hp_X]/1 mL; SILVER NITRATE 12 [hp_X]/1 mL; BAPTISIA TINCTORIA ROOT 12 [hp_X]/1 mL; BARIUM CHLORIDE DIHYDRATE 12 [hp_X]/1 mL; OYSTER SHELL CALCIUM CARBONATE, CRUDE 12 [hp_X]/1 mL; CAUSTICUM 12 [hp_X]/1 mL; CALCIUM SULFIDE 12 [hp_X]/1 mL; LACHESIS MUTA VENOM 12 [hp_X]/1 mL; MERCURIC CHLORIDE 12 [hp_X]/1 mL; DATURA STRAMONIUM 12 [hp_X]/1 mL; ACONITUM NAPELLUS WHOLE 12 [hp_X]/1 mL; GELSEMIUM SEMPERVIRENS ROOT 12 [hp_X]/1 mL; PHYTOLACCA AMERICANA ROOT 12 [hp_X]/1 mL
INACTIVE INGREDIENTS: WATER; ALCOHOL

DRUG FACTS:

ACTIVE INGREDIENTS:

Aconitum Napellus 12X, 18X, 24X, 30X, Agaricus Muscarius 12X, Ailanthus Glandulosus 12X, Allium Sativum 3X, Apis Mellifica 12X, Argentum Nitricum 12X, Baptisia Tinctoria 12X, Baryta Muriatica 12X, Calcarea Carbonica 12X, Causticum 12X, Chamomilla 6X, Echinacea (Angustifolia) 3X, 6X, 12X, 30X, Gelsemium Sempervirens 12X, 18X, 24X, 30X, Hepar Sulphuris Calcareum 12X, Kali Iodatum 6X, Lac Caninum 10X, Lachesis Mutus 12X, Mercurius Corrosivus 12X, Phytolacca Decandra 12X, 18X, 24X, 30X, Stramonium 12X.

PURPOSE:

Aconitum Napellus – Symptoms of Strep Infections, Agaricus Muscarius - Rash, Ailanthus Glandulosus - Nausea, Allium Sativum – Body Aches, Apis Mellifica - Rage, Argentum Nitricum - Anxiety, Baptisia Tinctoria - Impulsivity, Baryta Muriatica – Symptoms of Strep Infections, Calcarea Carbonica - Rash, Causticum - Nausea, Chamomilla – Body Aches, Echinacea (Angustifolia) - Anxiety, Gelsemium Sempervirens - Rage, Hepar Sulphuris Calcareum - Impulsivity, Kali Iodatum – Symptoms of Strep Infections, Lac Caninum - Rash, Lachesis Mutus - Nausea, Mercurius Corrosivus – Body Aches, Phytolacca Decandra - Rage, Stramonium - Anxiety

USES:

• For the temporary relief of symptoms including:

Symptoms of Strep Infections Rash Nausea Body Aches

Rage Anxiety Impulsivity

These statements are based upon homeopathic principles. They have not been reviewed by the Food and Drug Administration.

WARNINGS:

If pregnant or breast-feeding, ask a health professional before use.

Keep out of reach of children. In case of overdose, contact a physician or Poison Control Center right away.

Tamper Evident: Sealed for your protection. Do not use if seal is broken or missing.

KEEP OUT OF REACH OF CHILDREN:

In case of overdose, contact a physician or Poison Control Center right away.

DIRECTIONS:

1-10 drops under the tongue, 3 times a day or as directed by a health professional. Consult a physician for use in children under 12 years of age.

INACTIVE INGREDIENTS:

Demineralized water, 25% ethanol

QUESTIONS:

Dist. By: Deseret Biologicals, Inc.
469 W. Parkland Drive
Sandy, UT 84070

www.desbio.com

800-827-8204

PACKAGE LABEL DISPLAY:

Des Bio

STRE PLUS

Homeopathic

NDC 43742-1987-1

1 FL OZ (30 ml)